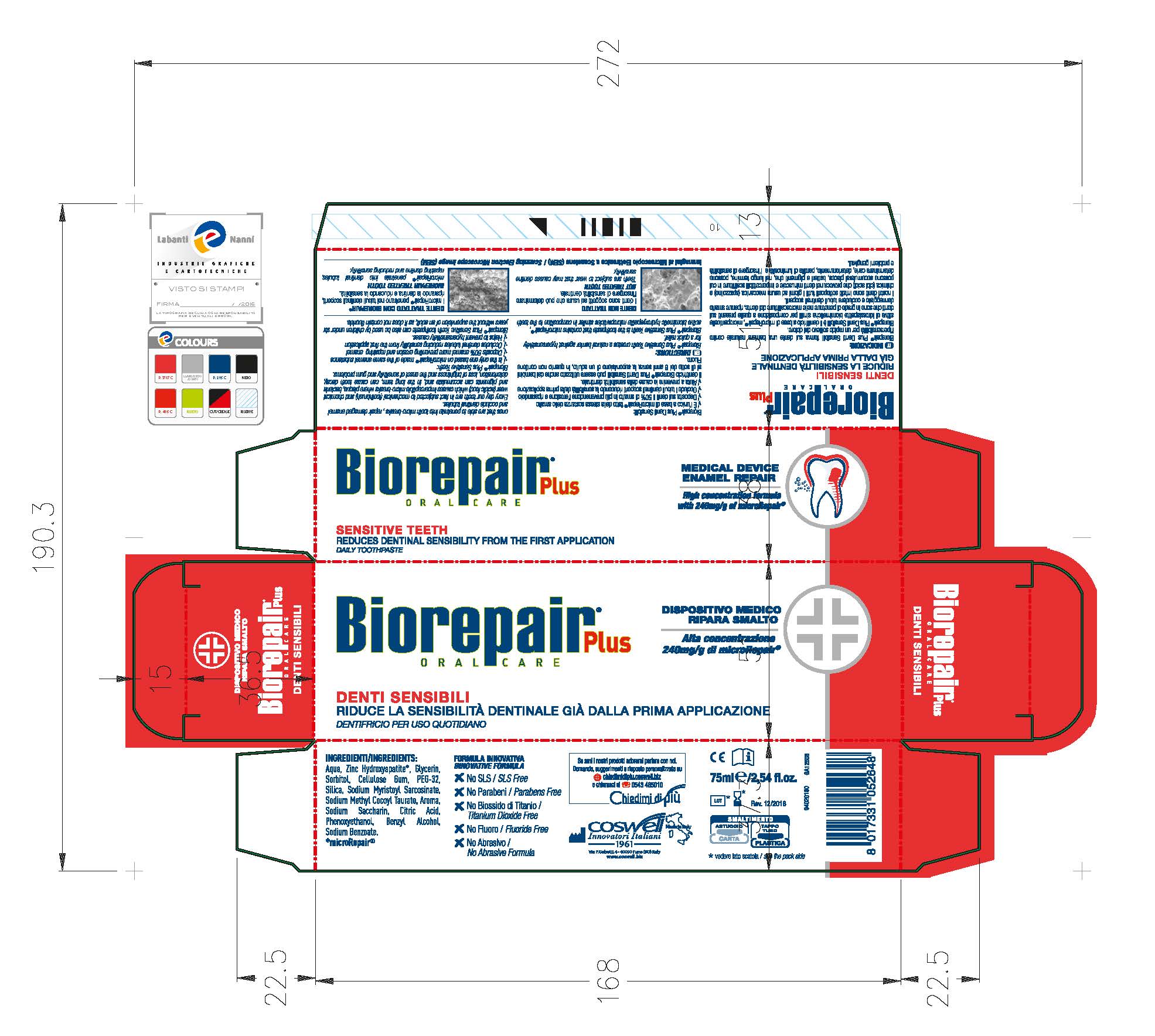 DRUG LABEL: Biorepair Sensitive Teeth
NDC: 70781-006 | Form: PASTE
Manufacturer: Coswell Spa
Category: otc | Type: HUMAN OTC DRUG LABEL
Date: 20170613

ACTIVE INGREDIENTS: DIBASIC CALCIUM PHOSPHATE DIHYDRATE 18.6 g/100 g
INACTIVE INGREDIENTS: HYDRATED SILICA; SODIUM MYRISTOYL SARCOSINATE; SODIUM METHYL COCOYL TAURATE; CITRIC ACID MONOHYDRATE; POLYETHYLENE GLYCOLS; BENZYL ALCOHOL; PHENOXYETHANOL; SACCHARIN SODIUM; SODIUM BENZOATE; CARBOXYMETHYLCELLULOSE SODIUM; GLYCERIN; WATER; SORBITOL

ACTIVE INGREDIENT

Contains:

Dicalcium Phosphate Dihydrate (0.6289 fl. oz.)

INACTIVE INGREDIENT

Ingredients:

Aqua, Glycerin, Sorbitol, Cellulose Gum, PEG-32, Silica, Sodium Myristoyl Sarcosinate, Sodium Methyl Cocyl Taurate, Aroma, Citric Acid, Sodium Saccharin, Benzyl Alcohol, Phenoxtethanol, Sodium Benzoate

PURPOSE

Biorepair Plus Sensitive Teeth creates a natural barrier against hypersensitivity for a quick relief.

Biorepair Plus Sensitive Teeth is the toothpaste that contains microRepair, active biomimetic hydroxyapatite microparticles similar in composition to the teeth ones that are able to penetrate into micro-breaks, repair damaged enamel and occlude dentinal tubules.

KEEP OUT OF REACH OF CHILDREN

Biorepair Plus Sensitive Teeth toothpaste can also be used by children under six years without the supervision of an adult, as it does not contain fluoride

DOSAGE AND ADMINISTRATION

For daily usage.

For daily usage.

Warnings